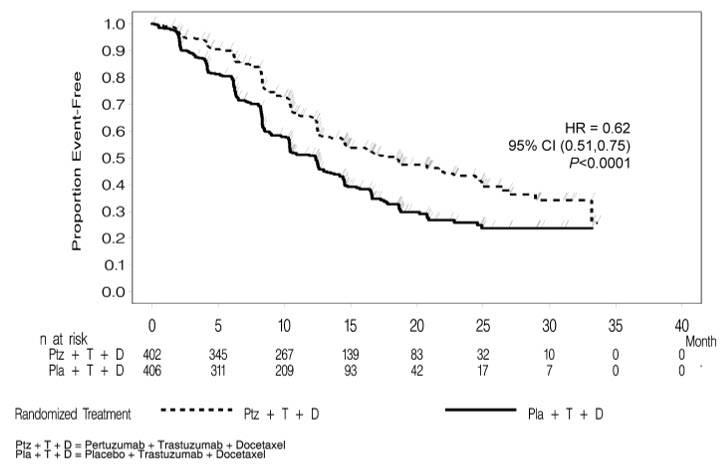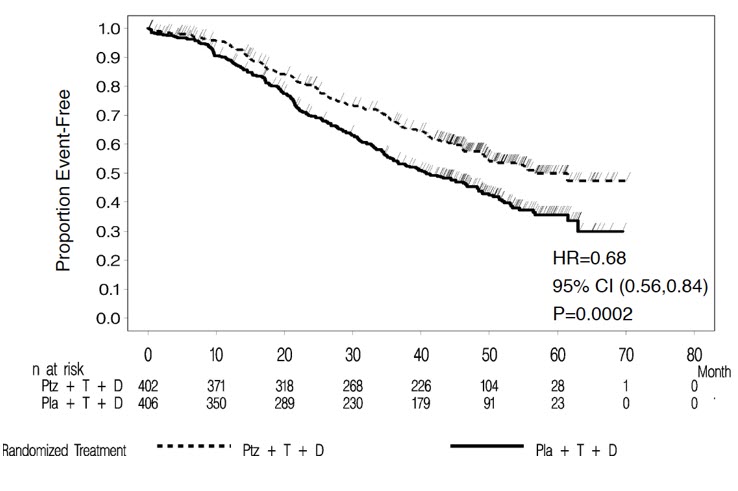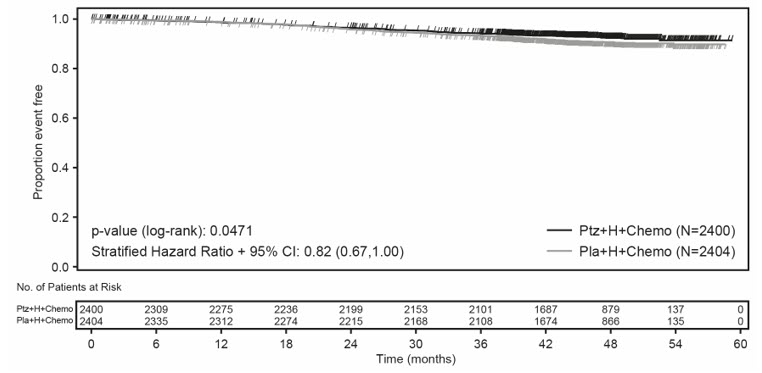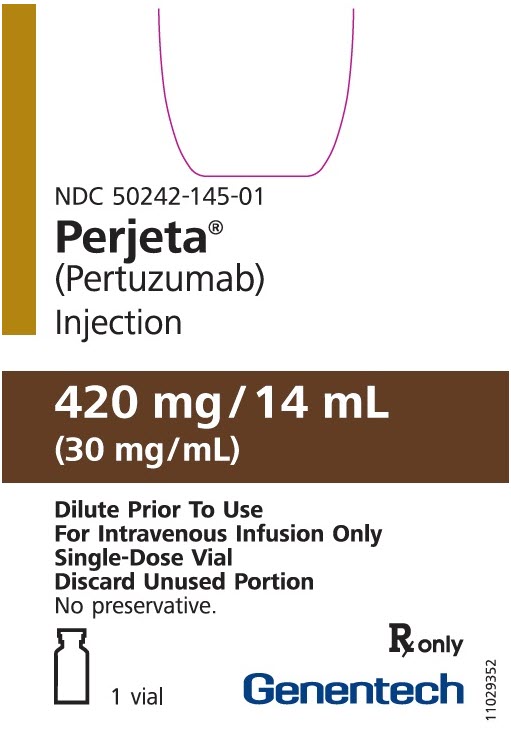 DRUG LABEL: PERJETA
NDC: 50242-145 | Form: INJECTION, SOLUTION, CONCENTRATE
Manufacturer: Genentech, Inc.
Category: prescription | Type: HUMAN PRESCRIPTION DRUG LABEL
Date: 20251205

ACTIVE INGREDIENTS: PERTUZUMAB 30 mg/1 mL
INACTIVE INGREDIENTS: HISTIDINE; ACETIC ACID; SUCROSE; POLYSORBATE 20; WATER

HIGHLIGHTS OF PRESCRIBING INFORMATION

These highlights do not include all the information needed to use PERJETA safely and effectively. See full prescribing information for PERJETA.
PERJETA® (pertuzumab) injection, for intravenous use
Initial U.S. Approval: 2012

WARNING: LEFT VENTRICULAR DYSFUNCTION and EMBRYO-FETAL TOXICITY

See full prescribing information for complete boxed warning.

- Left Ventricular Dysfunction: PERJETA can cause subclinical and clinical cardiac failure manifesting as decreased LVEF and CHF. Evaluate cardiac function prior to and during treatment. Discontinue PERJETA treatment for a confirmed clinically significant decrease in left ventricular function. (2.3, 5.1, 6.1)
- Embryo-fetal Toxicity: Exposure to PERJETA can cause embryo-fetal death and birth defects. Advise patients of these risks and the need for effective contraception. (5.2, 8.1, 8.3)

1 INDICATIONS AND USAGE

PERJETA is a HER2/neu receptor antagonist indicated for:

- Use in combination with trastuzumab and docetaxel for treatment of adults with HER2-positive metastatic breast cancer (MBC) who have not received prior anti-HER2 therapy or chemotherapy for metastatic disease. (1.1)
- Use in combination with trastuzumab and chemotherapy as
  - neoadjuvant treatment of adults with HER2-positive, locally advanced, inflammatory, or early stage breast cancer (either greater than 2 cm in diameter or node positive) as part of a complete treatment regimen for early breast cancer. (1.2, 2.2, 14.2)
  - adjuvant treatment of adults with HER2-positive early breast cancer at high risk of recurrence (1.2, 2.2, 14.3)

2 DOSAGE AND ADMINISTRATION

- For intravenous infusion only. Do not administer as an intravenous push or bolus. (2.5)
- HER2 testing: Perform using FDA-approved tests by laboratories with demonstrated proficiency. (2.1)
- The initial PERJETA dose is 840 mg administered as a 60-minute intravenous infusion, followed every 3 weeks thereafter by 420 mg administered as a 30 to 60 minute intravenous infusion. (2.3)
- MBC: Administer PERJETA, trastuzumab or trastuzumab hyaluronidase-oysk, and docetaxel every 3 weeks. (2.3)
- Neoadjuvant: Administer PERJETA, trastuzumab or trastuzumab hyaluronidase-oysk, and chemotherapy preoperatively every 3 weeks for 3 to 6 cycles. (2.3)
- Adjuvant: Administer PERJETA, trastuzumab or trastuzumab hyaluronidase-oysk, and chemotherapy postoperatively every 3 weeks for a total of 1 year (up to 18 cycles). (2.3)

3 DOSAGE FORMS AND STRENGTHS

- Injection: 420 mg/14 mL (30 mg/mL) solution in a single-dose vial. (3)

4 CONTRAINDICATIONS

PERJETA is contraindicated in patients with known hypersensitivity to pertuzumab or to any of its excipients. (4)

5 WARNINGS AND PRECAUTIONS

- Infusion-Related Reactions: PERJETA can cause serious infusion reactions, including fatal events: Monitor for signs and symptoms. If a significant infusion-associated reaction occurs, slow or interrupt the infusion and administer appropriate medical therapies. (5.3)
- Hypersensitivity Reactions/Anaphylaxis: PERJETA can cause hypersensitivity reactions, including anaphylaxis: Monitor for signs and symptoms, including angioedema. If a severe hypersensitivity reaction/anaphylaxis occurs, discontinue the infusion immediately and administer appropriate medical therapies. (5.4)

6 ADVERSE REACTIONS

Metastatic Breast Cancer

- The most common adverse reactions (> 30%) with PERJETA in combination with trastuzumab and docetaxel were diarrhea, alopecia, neutropenia, nausea, fatigue, rash, and peripheral neuropathy. (6.1)

Neoadjuvant Treatment of Breast Cancer

- The most common adverse reactions (> 30%) with PERJETA in combination with trastuzumab and docetaxel were alopecia, diarrhea, nausea, and neutropenia. (6.1)
- The most common adverse reactions (>30%) with PERJETA in combination with trastuzumab and docetaxel when given for 3 cycles following 3 cycles of FEC were fatigue, alopecia, diarrhea, nausea, vomiting, and neutropenia. (6.1)
- The most common adverse reactions (>30%) with PERJETA in combination with docetaxel, carboplatin, and trastuzumab (TCH) were fatigue, alopecia, diarrhea, nausea, vomiting, neutropenia, thrombocytopenia, and anemia. (6.1)
- The most common adverse reactions (>30%) with PERJETA in combination with trastuzumab and paclitaxel when given for 4 cycles following 4 cycles of ddAC were nausea, diarrhea, alopecia, fatigue, constipation, peripheral neuropathy, and headache. (6.1)
- The most common adverse reactions (>30%) with PERJETA in combination with trastuzumab and docetaxel when given for 4 cycles following 4 cycles of FEC were diarrhea, nausea, alopecia, asthenia, constipation, fatigue, mucosal inflammation, vomiting, myalgia, and anemia. (6.1)

Adjuvant Treatment of Breast Cancer

- The most common adverse reactions (>30%) with PERJETA in combination with trastuzumab and chemotherapy were diarrhea, nausea, alopecia, fatigue, peripheral neuropathy and vomiting. (6.1)

To report SUSPECTED ADVERSE REACTIONS, contact Genentech at 1-888-835-2555 or FDA at 1-800-FDA-1088 or www.fda.gov/medwatch.

8 USE IN SPECIFIC POPULATIONS

Females and Males of Reproductive Potential: Verify the pregnancy status of females prior to initiation of PERJETA. (8.3)

FULL PRESCRIBING INFORMATION

WARNING: LEFT VENTRICULAR DYSFUNCTION and EMBRYO-FETAL TOXICITY

- Left Ventricular Dysfunction: PERJETA can cause subclinical and clinical cardiac failure manifesting as decreased LVEF and CHF. Evaluate cardiac function prior to and during treatment. Discontinue PERJETA treatment for a confirmed clinically significant decrease in left ventricular function [see Dosage and Administration (2.3), Warnings and Precautions (5.1) and Adverse Reactions (6.1)].
- Embryo-fetal Toxicity: Exposure to PERJETA can cause embryo-fetal death and birth defects. Advise patients of these risks and the need for effective contraception [see Warnings and Precautions (5.2) and Use in Specific Populations (8.1) (8.3)].

1 INDICATIONS AND USAGE

1.1 Metastatic Breast Cancer (MBC)

PERJETA is indicated for use in combination with trastuzumab and docetaxel for the treatment of adults with HER2-positive metastatic breast cancer who have not received prior anti-HER2 therapy or chemotherapy for metastatic disease [see Dosage and Administration (2.2) and Clinical Studies (14.1)].

1.2 Early Breast Cancer (EBC)

PERJETA is indicated for use in combination with trastuzumab and chemotherapy for

- the neoadjuvant treatment of adults with HER2-positive, locally advanced, inflammatory, or early stage breast cancer (either greater than 2 cm in diameter or node positive) as part of a complete treatment regimen for early breast cancer [see Dosage and Administration (2.2) and Clinical Studies (14.2)].
- the adjuvant treatment of adults with HER2-positive early breast cancer at high risk of recurrence [see Dosage and Administration (2.2) and Clinical Studies (14.3)].

2 DOSAGE AND ADMINISTRATION

2.1 Evaluation and Testing Before Initiating Perjeta

Assess left ventricular ejection fraction (LVEF) prior to initiation of PERJETA and at regular intervals during treatment [see Boxed Warning, Dosage and Administration (2.4), Warnings and Precautions (5.1)].

Verify the pregnancy status of females of reproductive potential prior to the initiation of PERJETA [see Warnings and Precautions (5.2), Use in Specific Populations (8.1, 8.3)].

2.2 Patient Selection

Select patients based on HER2 protein overexpression or HER2 gene amplification in tumor specimens [see Indications and Usage (1) and Clinical Studies (14)]. Assessment of HER2 protein overexpression and HER2 gene amplification should be performed using FDA-approved tests specific for breast cancer by laboratories with demonstrated proficiency.

Information on the FDA-approved tests for the detection of HER2 protein overexpression and HER2 gene amplification is available at: http://www.fda.gov/CompanionDiagnostics.

Improper assay performance, including use of suboptimally fixed tissue, failure to utilize specified reagents, deviation from specific assay instructions, and failure to include appropriate controls for assay validation, can lead to unreliable results.

2.3 Recommended Dosage and Administration

The initial dose of PERJETA is 840 mg administered as a 60-minute intravenous infusion, followed every 3 weeks by a dose of 420 mg administered as an intravenous infusion over 30 to 60 minutes.

When administered with PERJETA, the recommended initial dose of trastuzumab is 8 mg/kg administered as a 90-minute intravenous infusion, followed every 3 weeks by a dose of 6 mg/kg administered as an intravenous infusion over 30 to 90 minutes.

When administered with PERJETA, the recommended initial dose of trastuzumab hyaluronidase-oysk is 600 mg/10,000 units (600 mg trastuzumab and 10,000 units hyaluronidase) administered subcutaneously over approximately 2 to 5 minutes once every three weeks irrespective of the patient's body weight.

Administer PERJETA, trastuzumab or trastuzumab hyaluronidase-oysk, and taxane sequentially. PERJETA and trastuzumab or trastuzumab hyaluronidase-oysk can be given in any order. Administer taxane after PERJETA and trastuzumab or trastuzumab hyaluronidase-oysk. An observation period of 30 to 60 minutes is recommended after each PERJETA infusion and before commencement of any subsequent administration of trastuzumab or trastuzumab hyaluronidase-oysk, or taxane [see Warnings and Precautions (5.3)].

In patients receiving an anthracycline-based regimen, administer PERJETA and trastuzumab or trastuzumab hyaluronidase-oysk after completion of the anthracycline.

Metastatic Breast Cancer (MBC)

When administered with PERJETA, the recommended initial dose of docetaxel is 75 mg/m^2 administered as an intravenous infusion. The dose may be escalated to 100 mg/m^2 administered every 3 weeks if the initial dose is well tolerated.

Neoadjuvant Treatment of Breast Cancer

Administer PERJETA every 3 weeks for 3 to 6 cycles as part of one of the following treatment regimens[see Clinical Studies (14.2, 14.3)]:

- Four preoperative cycles of PERJETA in combination with trastuzumab or trastuzumab hyaluronidase-oysk and docetaxel followed by 3 postoperative cycles of fluorouracil, epirubicin, and cyclophosphamide (FEC)
- Three or four preoperative cycles of FEC alone followed by 3 or 4 preoperative cycles of PERJETA in combination with docetaxel and trastuzumab or trastuzumab hyaluronidase-oysk
- Six preoperative cycles of PERJETA in combination with docetaxel, carboplatin, and trastuzumab (TCH) or trastuzumab hyaluronidase-oysk (escalation of docetaxel above 75 mg/m^2 is not recommended)
- Four preoperative cycles of dose-dense doxorubicin and cyclophosphamide (ddAC) alone followed by 4 preoperative cycles of PERJETA in combination with paclitaxel and trastuzumab or trastuzumab hyaluronidase-oysk

Following surgery, administer PERJETA and trastuzumab or trastuzumab hyaluronidase-oysk to complete 1 year of treatment (up to 18 cycles) or until disease recurrence or unmanageable toxicity, whichever occurs first.

Adjuvant Treatment of Breast Cancer

As part of a regimen including standard anthracycline- and/or taxane-based chemotherapy, administer PERJETA in combination with trastuzumab or trastuzumab hyaluronidase-oysk every 3 weeks for a total of 1 year (up to 18 cycles) or until disease recurrence or unmanageable toxicity, whichever occurs first. Administer PERJETA on Day 1 of the first taxane-containing cycle [see Clinical Studies (14.3)].

2.4 Important Dosing Considerations

Missed Dose

The recommended dosage modifications for delayed or missed doses are listed in Table 1.

Table 1: Recommendations for Delayed or Missed Doses
Time between two sequential doses | PERJETA | Trastuzumab (intravenous) | Trastuzumab hyaluronidase-oysk
< 6 weeks | Administer PERJETA 420 mg intravenously as soon as possible. Do not wait until the next planned dose. | Administer trastuzumab 6 mg/kg intravenously as soon as possible. Do not wait until the next planned dose. | Administer trastuzumab hyaluronidase-oysk 600 mg/10,000 units subcutaneously as soon as possible. Do not wait until the next planned dose.
≥ 6 weeks | Readminister PERJETA loading dose of 840 mg intravenously as a 60 minute infusion, followed by a maintenance dose of 420 mg administered intravenously over a period of 30 to 60 minutes every 3 weeks thereafter. | Readminister trastuzumab loading dose of 8 mg/kg intravenously over approximately 90 minutes, followed by a maintenance dose of 6 mg/kg administered intravenously over a period of 30 or 90 minutes every 3 weeks thereafter. | Administer trastuzumab hyaluronidase-oysk 600 mg/10,000 units subcutaneously as soon as possible. Do not wait until the next planned dose.

Permanently discontinue PERJETA if trastuzumab or trastuzumab hyaluronidase-oysk treatment is discontinued.

Dose reductions are not recommended for PERJETA.

For chemotherapy dose modifications, see relevant prescribing information.

2.5 Dosage Modification for Adverse Reactions

Left Ventricular Dysfunction

Assess left ventricular ejection fraction (LVEF) prior to initiation of PERJETA and at regular intervals during treatment. The recommended dosage modifications for LVEF decrease are listed in Table 2 [see Warnings and Precautions (5.1)].

Table 2: Dose Modifications for Left Ventricular Dysfunction
 | Pre-treatment LVEF: | Monitor LVEF every: | Withhold PERJETA and trastuzumab or trastuzumab hyaluronidase-oysk for at least 3 weeks for an LVEF decrease to: |  | Resume PERJETA and trastuzumab or trastuzumab hyaluronidase-oysk after 3 weeks if LVEF has recovered to:
Metastatic Breast Cancer | ≥ 50% | ~12 weeks | Either |  | Either
Metastatic Breast Cancer | ≥ 50% | ~12 weeks | <40% | 40%-45% with a fall of ≥10%-points below pre-treatment value | >45% | 40%-45% with a fall of <10%-points below pre-treatment value
Early Breast Cancer | ≥ 55% [For patients receiving anthracycline-based chemotherapy, a LVEF of ≥ 50% is required after completion of anthracyclines, before starting PERJETA and trastuzumab or trastuzumab hyaluronidase-oysk.] | ~12 weeks (once during neoadjuvant therapy) | <50% with a fall of ≥10%-points below pre-treatment value |  | Either
Early Breast Cancer | ≥ 55% [For patients receiving anthracycline-based chemotherapy, a LVEF of ≥ 50% is required after completion of anthracyclines, before starting PERJETA and trastuzumab or trastuzumab hyaluronidase-oysk.] | ~12 weeks (once during neoadjuvant therapy) | <50% with a fall of ≥10%-points below pre-treatment value |  | ≥50% | <10% points below pre-treatment value

Infusion-Related Reactions

The infusion rate of PERJETA may be slowed or interrupted if the patient develops an infusion-related reaction [see Warnings and Precautions (5.3)].

Hypersensitivity Reactions/Anaphylaxis

The infusion should be discontinued immediately if the patient experiences a serious hypersensitivity reaction [see Warnings and Precautions (5.4)].

2.6 Preparation for Administration

Administer as an intravenous infusion only. Do not administer as an intravenous push or bolus. Do not mix PERJETA with other drugs.

Preparation

Prepare the solution for infusion, using aseptic technique, as follows:

- Parenteral drug products should be inspected visually for particulates and discoloration prior to administration, whenever solution and container permit.
- Withdraw the appropriate volume of PERJETA solution from the vial(s) using a sterile needle and syringe.
- Dilute into a 250 mL 0.45% Sodium Chloride Injection or 0.9% Sodium Chloride Injection infusion bag.
- Mix diluted solution by gentle inversion. Do not shake.
- Administer immediately once prepared.
- If the diluted infusion solution is not used immediately, it can be stored refrigerated at 2°C to 8°C (36 °F to 46 °F) for up to 24 hours.
- Dilute with 0.45% Sodium Chloride Injection or 0.9% Sodium Chloride Injection only. Do not use 5% Dextrose Injection.

3 DOSAGE FORMS AND STRENGTHS

Injection: 420 mg/14 mL (30 mg/mL) clear to slightly opalescent and colorless to pale brown solution in a single-dose vial

4 CONTRAINDICATIONS

PERJETA is contraindicated in patients with known hypersensitivity to pertuzumab or to any of its excipients [see Warnings and Precautions (5.4)].

5 WARNINGS AND PRECAUTIONS

5.1 Left Ventricular Dysfunction

PERJETA can cause left ventricular dysfunction, including symptomatic heart failure. Decreases in LVEF have been reported with drugs that block HER2 activity, including PERJETA.

Assess LVEF prior to initiation of PERJETA and at regular intervals during treatment to ensure that LVEF is within normal limits. If the LVEF declines and has not improved, or has declined further at the subsequent assessment, consider permanent discontinuation of PERJETA and trastuzumab [see Dosage Modification for Adverse Reactions (2.5)].

In the PERJETA-treated patients with MBC in CLEOPATRA, left ventricular dysfunction occurred in 4% of patients and symptomatic left ventricular systolic dysfunction (LVSD) (congestive heart failure) occurred in 1% of patients. Patients who received prior anthracyclines or prior radiotherapy to the chest area may be at higher risk of decreased LVEF or left ventricular dysfunction.

In patients receiving PERJETA as a neoadjuvant treatment in combination with trastuzumab and docetaxel in NeoSphere, LVEF decline > 10% and a drop to < 50% occurred in 8% of patients and left ventricular dysfunction occurred in 3% of patients. LVEF recovered to ≥ 50% in all these patients.

In patients receiving neoadjuvant PERJETA in TRYPHAENA, LVEF decline > 10% and a drop to < 50% occurred in 7% of patients treated with PERJETA plus trastuzumab and FEC followed by PERJETA plus trastuzumab and docetaxel, 16% of patients treated with PERJETA plus trastuzumab and docetaxel following FEC, and 11% of patients treated with PERJETA in combination with TCH. Left ventricular dysfunction occurred in 6% of patients treated with PERJETA plus trastuzumab and FEC followed by PERJETA plus trastuzumab and docetaxel, 4% of patients treated with PERJETA plus trastuzumab and docetaxel following FEC, and 3% of patients treated with PERJETA in combination with TCH. Symptomatic LVSD occurred in 4% of patients treated with PERJETA plus trastuzumab and docetaxel following FEC, 1% of patients treated with PERJETA in combination with TCH, and none of the patients treated with PERJETA plus trastuzumab and FEC followed by PERJETA plus trastuzumab and docetaxel. LVEF recovered to ≥ 50% in all but one patient.

In patients receiving neoadjuvant PERJETA in BERENICE, in the neoadjuvant period, LVEF decline ≥ 10% and a drop to < 50% as measured by ECHO/MUGA assessment occurred in 7% of patients treated with PERJETA plus trastuzumab and paclitaxel following ddAC, and 2% of patients treated with PERJETA plus trastuzumab and docetaxel following FEC. Ejection fraction decreased (asymptomatic LVD) occurred in 7% of patients treated with PERJETA plus trastuzumab and paclitaxel following ddAC and 4% of the patients treated with PERJETA plus trastuzumab and docetaxel following FEC in the neoadjuvant period. Symptomatic LVSD (NYHA Class III/IV Congestive Heart Failure) occurred in 2% of patients treated with PERJETA plus trastuzumab and paclitaxel following ddAC and none of the patients treated with PERJETA plus trastuzumab and docetaxel following FEC in the neoadjuvant period.

In patients receiving adjuvant PERJETA in APHINITY, the incidence of symptomatic heart failure (NYHA Class III/IV) with a LVEF decline ≥ 10% and a drop to < 50% was 0.6%. Of the patients who experienced symptomatic heart failure, 47% of PERJETA-treated patients had recovered (defined as 2 consecutive LVEF measurements above 50%) at the data cutoff. The majority of the events (86%) were reported in anthracycline-treated patients. Asymptomatic or mildly symptomatic (NYHA Class II) declines in LVEF ≥ 10% and a drop to < 50% were reported in 3% of PERJETA-treated patients, of whom 80% recovered at the data cutoff.

PERJETA has not been studied in patients with a pretreatment LVEF value of < 50%, a prior history of CHF, decreases in LVEF to < 50% during prior trastuzumab therapy, or conditions that could impair left ventricular function such as uncontrolled hypertension, recent myocardial infarction, serious cardiac arrhythmia requiring treatment or a cumulative prior anthracycline exposure to > 360 mg/m^2 of doxorubicin or its equivalent.

5.2 Embryo-Fetal Toxicity

Based on its mechanism of action and findings in animal studies, PERJETA can cause fetal harm when administered to a pregnant woman. PERJETA is a HER2/neu receptor antagonist. Cases of oligohydramnios and oligohydramnios sequence manifesting as pulmonary hypoplasia, skeletal abnormalities, and neonatal death have been reported with use of another HER2/neu receptor antagonist (trastuzumab) during pregnancy. In an animal reproduction study, administration of pertuzumab to pregnant cynomolgus monkeys during the period of organogenesis resulted in oligohydramnios, delayed fetal kidney development, and embryo-fetal death at exposures 2.5 to 20 times the exposure in humans at the recommended dose, based on Cmax.

Verify the pregnancy status of females of reproductive potential prior to the initiation of PERJETA. Advise pregnant women and females of reproductive potential that exposure to PERJETA in combination with trastuzumab during pregnancy or within 7 months prior to conception can result in fetal harm, including embryo-fetal death or birth defects. Advise females of reproductive potential to use effective contraception during treatment and for 7 months following the last dose of PERJETA in combination with trastuzumab [see Use in Specific Populations (8.1, 8.3)].

5.3 Infusion-Related Reactions

PERJETA can cause serious infusion reactions, including fatal events [see Adverse Reactions (6.1)].

In CLEOPATRA, on the first day, when only PERJETA was administered, infusion-related reactions occurred in 13% of patients and < 1% were Grade 3 or 4. The most common infusion reactions (≥ 1%) were pyrexia, chills, fatigue, headache, asthenia, hypersensitivity, and vomiting. During the second cycle when all drugs were administered on the same day, the most common infusion reactions in the PERJETA-treated group (≥ 1%) were fatigue, dysgeusia, hypersensitivity, myalgia, and vomiting.

In APHINITY, when PERJETA was administered in combination with trastuzumab and chemotherapy on the same day, infusion-related reactions occurred in 21% of patients with <1% of patients experiencing Grade 3-4 events.

Observe patients closely for 60 minutes after the first infusion and for 30 minutes after subsequent infusions of PERJETA. If a significant infusion-related reaction occurs, slow or interrupt the infusion, and administer appropriate medical therapies. Monitor patients carefully until complete resolution of signs and symptoms. Consider permanent discontinuation in patients with severe infusion reactions [see Dosage and Administration (2.5)].

5.4 Hypersensitivity Reactions/Anaphylaxis

PERJETA can cause hypersensitivity reactions, including anaphylaxis.

In CLEOPATRA, the overall frequency of hypersensitivity/anaphylaxis reactions was 11% in PERJETA-treated patients, with Grade 3 – 4 hypersensitivity reactions and anaphylaxis occurring in 2% of patients.

In NeoSphere, TRYPHAENA, BERENICE, and APHINITY, hypersensitivity/anaphylaxis events were consistent with those observed in CLEOPATRA. In APHINITY, the overall frequency of hypersensitivity/anaphylaxis was 5% in the PERJETA treated group. The incidence was highest in the PERJETA plus TCH treated group (8%) with 1% Grade 3 – 4 events.

Observe patients closely for hypersensitivity reactions. Severe hypersensitivity, including anaphylaxis and fatal events, have been observed in patients treated with PERJETA [see Clinical Trials Experience (6.1)]. Angioedema has been described in post-marketing reports. Medications to treat such reactions, as well as emergency equipment, should be available for immediate use prior to administration of PERJETA. PERJETA is contraindicated in patients with known hypersensitivity to pertuzumab or to any of its excipients [see Contraindications (4)].

6 ADVERSE REACTIONS

The following adverse reactions are discussed in greater detail in other sections of the label:

- Left Ventricular Dysfunction [see Warnings and Precautions (5.1)]
- Embryo-Fetal Toxicity [see Warnings and Precautions (5.2)]
- Infusion-Related Reactions [see Warnings and Precautions (5.3)]
- Hypersensitivity Reactions/Anaphylaxis [see Warnings and Precautions (5.4)]

6.1 Clinical Trials Experience

Because clinical trials are conducted under widely varying conditions, adverse reaction rates observed in the clinical trials of a drug cannot be directly compared to rates in the clinical trials of another drug and may not reflect the rates observed in clinical practice.

Metastatic Breast Cancer (MBC)

CLEOPATRA

The safety of PERJETA in combination with trastuzumab and docetaxel was evaluated in a randomized trial (CLEOPATRA) in patients with HER2-positive metastatic breast cancer [see Clinical Studies (14.1)]. Patients received either PERJETA administered at an initial dose of 840 mg followed by 420 mg every 3 weeks thereafter or placebo in combination with trastuzumab (initial dose of 8 mg/kg, followed by 6 mg/kg every 3 weeks thereafter) and docetaxel (75 mg/m2 by intravenous infusion every 3 weeks for 6 cycles). The median duration of study treatment was 18.1 months for patients in the PERJETA-treated group.

Permanent discontinuation of PERJETA, trastuzumab, and docetaxel due to adverse reactions occurred in 6% of patients. Adverse reactions that led to permanent discontinuation of PERJETA, trastuzumab, and docetaxel in >1% of patients were left ventricular dysfunction.

The safety profile of PERJETA remained unchanged with an additional 2.75 years of follow-up (median total follow-up of 50 months) in CLEOPATRA.

The most common adverse reactions (> 30%) with PERJETA in combination with trastuzumab and docetaxel were diarrhea, alopecia, neutropenia, nausea, fatigue, rash, and peripheral neuropathy. The most common Grade 3 – 4 adverse reactions (> 2%) were neutropenia, febrile neutropenia, leukopenia, diarrhea, peripheral neuropathy, anemia, asthenia, and fatigue. An increased incidence of febrile neutropenia was observed for Asian patients in both treatment arms compared with patients of other races and from other geographic regions. Among Asian patients, the incidence of febrile neutropenia was higher in the pertuzumab-treated group (26%) compared with the placebo-treated group (12%).

Table 3 summarizes the adverse reactions in CLEOPATRA that occurred ≥ 10% of patients in the PERJETA-treated group.

Table 3: Adverse Reactions (≥ 10%) in Patients Who Received PERJETA in Combination with Trastuzumab and Docetaxel in CLEOPATRA
Adverse Reactions | PERJETA + trastuzumab + docetaxel n=407 % |  | Placebo + trastuzumab + docetaxel n=397 %
 | All Grades % | Grades 3 – 4 % | All Grades % | Grades 3 – 4 %
Gastrointestinal disorders
Diarrhea | 67 | 8 | 46 | 5
Nausea | 42 | 1 | 42 | 0.5
Vomiting | 24 | 1 | 24 | 2
Stomatitis | 19 | 0.5 | 15 | 0.3
Constipation | 15 | 0 | 25 | 1
Skin and subcutaneous tissue disorders
Alopecia | 61 | 0 | 60 | 0.3
Rash | 34 | 0.7 | 24 | 0.8
Nail disorder | 23 | 1 | 23 | 0.3
Pruritus | 14 | 0 | 10 | 0
Dry skin | 11 | 0 | 4 | 0
Blood and lymphatic system disorders
Neutropenia | 53 | 49 | 50 | 46
Anemia | 23 | 2 | 19 | 4
Leukopenia | 18 | 12 | 20 | 15
Febrile neutropenia [In this table this denotes an adverse reaction that has been reported in association with a fatal outcome] | 14 | 13 | 8 | 7
General disorders and administration site conditions
Fatigue | 37 | 2 | 37 | 3
Mucosal inflammation | 28 | 1 | 20 | 1
Asthenia | 26 | 2 | 30 | 2
Peripheral edema | 23 | 0.5 | 30 | 0.8
Pyrexia | 19 | 1 | 18 | 0.5
Nervous system disorders
Neuropathy peripheral | 32 | 3 | 34 | 2
Headache | 21 | 1 | 17 | 0.5
Dysgeusia | 18 | 0 | 16 | 0
Dizziness | 13 | 0.5 | 12 | 0
Metabolism and nutrition disorders
Decreased appetite | 29 | 2 | 26 | 2
Musculoskeletal and connective tissue disorders
Myalgia | 23 | 1 | 24 | 0.8
Arthralgia | 15 | 0.2 | 16 | 0.8
Infections and infestations
Upper respiratory tract infection | 17 | 0.7 | 13 | 0
Nasopharyngitis | 12 | 0 | 13 | 0.3
Respiratory, thoracic, and mediastinal disorders
Dyspnea | 14 | 1 | 16 | 2
Eye disorders
Lacrimation increased | 14 | 0 | 14 | 0
Psychiatric disorders
Insomnia | 13 | 0 | 13 | 0

Clinically relevant adverse reactions in < 10% of patients in the PERJETA-treated group in CLEOPATRA included paronychia (7%).

Adverse Reactions Reported in Patients Receiving PERJETA and Trastuzumab After Discontinuation of Docetaxel

In CLEOPATRA, adverse reactions that occurred after discontinuation of docetaxel included diarrhea (19%), upper respiratory tract infection (13%), rash (12%), headache (11%), and fatigue (11%).

Neoadjuvant Treatment of Breast Cancer

NeoSphere

The safety of PERJETA was evaluated in a randomized trial (NeoSphere) in patients with operable, locally advanced, or inflammatory HER2-positive breast cancer (T2-4d) who were scheduled for neoadjuvant therapy [see Clinical Studies (14.2)].

In combination with trastuzumab and docetaxel, PERJETA was given intravenously at an initial dose of 840 mg, followed by 420 mg every 3 weeks for 4 cycles. After surgery, patients in the PERJETA plus trastuzumab arm received docetaxel every 3 weeks for 4 cycles prior to FEC.

Permanent discontinuation of neoadjuvant PERJETA due to an adverse reaction occurred in 0.9% of patients.

The most common adverse reactions (> 30%) were alopecia, neutropenia, diarrhea, and nausea. The most common Grade 3 – 4 adverse reactions (> 2%) were neutropenia, febrile neutropenia, leukopenia, and diarrhea.

Table 4 summarizes the adverse reactions in NeoSphere that occurred ≥ 10% of patients who received neoadjuvant PERJETA with trastuzumab and docetaxel followed by FEC.

Table 4: Adverse Reactions (≥ 10%) in Patients who Received Neoadjuvant PERJETA in NeoSphere
Adverse Reactions | Trastuzumab + docetaxel n=107 % |  | PERJETA + trastuzumab + docetaxel n=107 %
 | All Grades % | Grades 3 – 4 % | All Grades % | Grades 3 – 4 %
Skin and subcutaneous tissue disorders
Alopecia | 66 | 0 | 65 | 0
Rash | 21 | 2 | 26 | 0.9
Blood and lymphatic system disorders
Neutropenia | 64 | 59 | 50 | 45
Leukopenia | 21 | 11 | 9 | 5
Gastrointestinal disorders
Nausea | 36 | 0 | 39 | 0
Diarrhea | 34 | 4 | 46 | 6
Vomiting | 12 | 0 | 13 | 0
Stomatitis | 7 | 0 | 18 | 0
General disorders and administration site conditions
Fatigue | 27 | 0 | 26 | 0.9
Mucosal inflammation | 21 | 0 | 26 | 2
Asthenia | 18 | 0 | 21 | 2
Pyrexia | 10 | 0 | 17 | 0
Peripheral edema | 10 | 0 | 3 | 0
Musculoskeletal and connective tissue disorders
Myalgia | 22 | 0 | 22 | 0
Arthralgia | 8 | 0 | 10 | 0
Nervous system disorders
Peripheral Sensory Neuropathy | 12 | 0.9 | 8 | 0.9
Headache | 11 | 0 | 11 | 0
Dysgeusia | 10 | 0 | 15 | 0
Psychiatric disorders
Insomnia | 11 | 0 | 8 | 0
Metabolism and nutrition disorders
Decreased appetite | 7 | 0 | 14 | 0

Clinically relevant adverse reactions in < 10% of patients receiving neoadjuvant PERJETA with trastuzumab and docetaxel followed by FEC included anemia, febrile neutropenia, dizziness, upper respiratory tract infection, and increased lacrimation.

Neoadjuvant Treatment of Breast Cancer

TRYPHAENA

The safety of PERJETA was evaluated in patients with HER2-positive locally advanced, operable, or inflammatory (T2-4d) breast cancer in TRYPHAENA [see Clinical Studies (14.2)].

Adverse reactions resulting in permanent discontinuation of any component of neoadjuvant treatment occurred in 7% of patients receiving PERJETA in combination with trastuzumab and docetaxel following FEC and 8% for patients receiving PERJETA in combination with TCH.

The most common adverse reactions (>2%) resulting in permanent discontinuation of PERJETA were left ventricular dysfunction, drug hypersensitivity, and neutropenia.

For PERJETA administered in combination with trastuzumab and docetaxel for 3 cycles following 3 cycles of FEC, the most common adverse reactions (> 30%) were diarrhea, nausea, alopecia, neutropenia, vomiting, and fatigue. The most common Grade 3 – 4 adverse reactions (> 2%) were neutropenia, leukopenia, febrile neutropenia, diarrhea, left ventricular dysfunction, anemia, dyspnea, nausea, and vomiting.

For PERJETA administered in combination with docetaxel, carboplatin, and trastuzumab (TCH) for 6 cycles, the most common adverse reactions (> 30%) were diarrhea, alopecia, neutropenia, nausea, fatigue, vomiting, anemia, and thrombocytopenia. The most common Grade 3 – 4 adverse reactions (> 2%) were neutropenia, febrile neutropenia, anemia, leukopenia, diarrhea, thrombocytopenia, vomiting, fatigue, ALT increased, hypokalemia, and hypersensitivity.

Table 5 summarizes the adverse reactions in TRYPHAENA that occurred in > 10% of patients who received neoadjuvant PERJETA with trastuzumab and docetaxel following FEC or who received neoadjuvant PERJETA in combination with TCH.

Table 5: Adverse Reactions (≥ 10%) in Patients Receiving Neoadjuvant Treatment with PERJETA in TRYPHAENA
Adverse Reactions | PERJETA + trastuzumab + docetaxel following FEC |  | PERJETA + TCH
Adverse Reactions | n=75 % |  | n=76 %
 | All Grades % | Grades 3 – 4 % | All Grades % | Grades 3 – 4 %
Gastrointestinal disorders
Diarrhea | 61 | 5 | 72 | 12
Nausea | 53 | 3 | 45 | 0
Vomiting | 36 | 3 | 39 | 5
Dyspepsia | 8 | 0 | 22 | 0
Constipation | 23 | 0 | 16 | 0
Stomatitis | 17 | 0 | 12 | 0
Skin and subcutaneous tissue disorders
Alopecia | 52 | 0 | 55 | 0
Rash | 11 | 0 | 21 | 1
Palmar-Plantar Erythrodysaesthesia Syndrome | 11 | 0 | 8 | 0
Dry skin | 9 | 0 | 11 | 0
Blood and lymphatic system disorders
Neutropenia | 47 | 43 | 49 | 46
Leukopenia | 16 | 12 | 17 | 12
Anemia | 9 | 4 | 38 | 17
Febrile neutropenia | 9 | 9 | 17 | 17
Thrombocytopenia | 1 | 0 | 30 | 12
General disorders and administration site conditions
Fatigue | 36 | 0 | 42 | 4
Mucosal inflammation | 20 | 0 | 17 | 1
Pyrexia | 9 | 0 | 16 | 0
Asthenia | 15 | 1 | 13 | 1
Edema peripheral | 4 | 0 | 9 | 0
Psychiatric disorders
Insomnia | 13 | 0 | 21 | 0
Nervous system disorders
Headache | 15 | 0 | 17 | 0
Dysgeusia | 13 | 0 | 21 | 0
Dizziness | 8 | 1 | 16 | 0
Neuropathy peripheral | 1 | 0 | 11 | 0
Metabolism and nutrition disorders
Decreased appetite | 11 | 0 | 21 | 0
Respiratory, thoracic, and mediastinal disorders
Epistaxis | 11 | 0 | 16 | 1
Dyspnea | 8 | 3 | 11 | 1
Oropharyngeal pain | 7 | 0 | 12 | 0
Cough | 5 | 0 | 12 | 0
Musculoskeletal and connective tissue disorders
Myalgia | 11 | 1 | 11 | 0
Arthralgia | 12 | 0 | 7 | 0
Eye disorders
Lacrimation increased | 5 | 0 | 8 | 0
Investigations
ALT increased | 3 | 0 | 11 | 4
Immune system disorders
Hypersensitivity | 1 | 0 | 12 | 3

Clinically relevant adverse reactions in < 10% of patients who received neoadjuvant PERJETA with trastuzumab and docetaxel following FEC or who received neoadjuvant PERJETA in combination with TCH included nail disorder, paronychia, pruritus, upper respiratory tract infection, and nasopharyngitis.

Neoadjuvant Treatment of Breast Cancer

BERENICE

The safety of PERJETA was evaluated in a two-arm non-randomized study (BERENICE) in patient with HER2-positive locally advanced, inflammatory, or early-stage HER2-positive breast cancer [see Clinical Studies (14.2)].

Adverse reactions resulting in permanent discontinuation of any component of neoadjuvant treatment were 14% for patients receiving PERJETA in combination with trastuzumab and paclitaxel following ddAC and 8% for patients receiving PERJETA in combination with trastuzumab and docetaxel following FEC. The most common adverse reactions (>1%) resulting in permanent discontinuation of any component of neoadjuvant treatment were peripheral neuropathy, decreased ejection fraction, diarrhea, neutropenia and infusion-related reaction.

For PERJETA administered in combination with trastuzumab and paclitaxel for 4 cycles following 4 cycles of ddAC, the most common adverse reactions (> 30%) were nausea, diarrhea, alopecia, fatigue, constipation, peripheral neuropathy and headache. The most common Grade 3 – 4 adverse reactions (> 2%) were neutropenia, febrile neutropenia, decreased neutrophil count, decreased white blood cell count, anemia, diarrhea, peripheral neuropathy, increased ALT, and nausea.

For PERJETA administered in combination with trastuzumab and docetaxel for 4 cycles following 4 cycles of FEC, the most common adverse reactions (> 30%) were diarrhea, nausea, alopecia, asthenia, constipation, fatigue, mucosal inflammation, vomiting, myalgia, and anemia. The most common Grade 3 – 4 adverse reactions (> 2%) were febrile neutropenia, diarrhea, neutropenia, decreased neutrophil count stomatitis, fatigue, vomiting, mucosal inflammation, neutropenic sepsis and anemia.

Table 6 summarizes the adverse reactions in BERENICE that occurred in ≥ 10% of patients who received neoadjuvant PERJETA with trastuzumab and paclitaxel following ddAC or who received neoadjuvant PERJETA with trastuzumab and docetaxel following FEC.

Table 6: Adverse Reactions (≥ 10%) of Patients Receiving Neoadjuvant PERJETA in Combination with Trastuzumab and Taxane Chemotherapy Following ddAC or FEC in BERENICE
Adverse Reactions | PERJETA + trastuzumab + paclitaxel following ddAC n=199 % |  | PERJETA + trastuzumab + docetaxel following FEC n=198 %
 | All Grades % | Grades 3 – 4 % | All Grades % | Grades 3 – 4 %
Gastrointestinal disorders
Nausea | 71 | 3 | 69 | 2
Diarrhea | 67 | 3 | 69 | 10
Constipation | 35 | 0.5 | 38 | 0.5
Vomiting | 23 | 1 | 35 | 4
Stomatitis | 25 | 0 | 27 | 5
Dyspepsia | 19 | 0 | 16 | 0
Upper abdominal pain | 6 | 0 | 13 | 0
Abdominal pain | 5 | 0 | 10 | 0
Gastroesophageal reflux disease | 12 | 0 | 2 | 0
Skin and subcutaneous tissue disorders
Alopecia | 62 | 0 | 59 | 0
Rash | 14 | 0 | 11 | 0
Dry skin | 14 | 0 | 10 | 0
Nail discoloration | 15 | 0 | 2 | 0
Palmar-Plantar Erythrodysaesthesia Syndrome | 6 | 0 | 10 | 0.5
General disorders and administration site conditions
Fatigue | 58 | 1 | 38 | 5
Asthenia | 19 | 2 | 41 | 0
Mucosal inflammation | 22 | 1 | 37 | 4
Pyrexia | 15 | 0 | 18 | 0
Peripheral edema | 9 | 0 | 12 | 1
Nervous system disorders
Peripheral neuropathy | 42 | 3 | 26 | 0.5
Headache | 30 | 0.5 | 14 | 0.5
Dysgeusia | 20 | 0 | 19 | 0.5
Paresthesia | 15 | 0 | 9 | 0
Dizziness | 12 | 0 | 8 | 0
Blood and lymphatic system disorders
Anemia | 27 | 3 | 30 | 3
Neutropenia | 22 | 12 | 16 | 9
Febrile neutropenia | 7 | 7 | 17 | 17
Musculoskeletal and connective tissue disorders
Myalgia | 20 | 0 | 33 | 1
Arthralgia | 20 | 0 | 21 | 1
Back pain | 10 | 0 | 9 | 0
Pain in extremity | 10 | 0 | 8 | 0
Bone pain | 12 | 0.5 | 5 | 0
Respiratory, thoracic, and mediastinal disorders
Epistaxis | 25 | 0 | 19 | 0
Dyspnea | 15 | 0.5 | 15 | 0.5
Cough | 20 | 0.5 | 9 | 0
Oropharyngeal pain | 10 | 0 | 8 | 0.5
Metabolism and nutrition disorders
Decreased appetite | 20 | 0 | 23 | 0
Psychiatric disorders
Insomnia | 19 | 0 | 13 | 0
Vascular disorders
Hot flush | 19 | 0 | 13 | 0
Injury, poisoning and procedural complications
Infusion-related reaction | 16 | 1 | 13 | 1
Eye disorders
Increased lacrimation | 9 | 0 | 18 | 0
Investigations
Decreased white blood cell count | 11 | 4 | 3 | 2
Infections and infestations
Urinary tract infection | 11 | 1 | 2 | 0

Clinically relevant adverse reactions in < 10% of patients who received PERJETA in combination with trastuzumab and paclitaxel following ddAC or patients receiving PERJETA in combination with trastuzumab and docetaxel following FEC included pruritus, nail disorder, paronychia, upper respiratory tract infection, and nasopharyngitis.

Adjuvant Treatment of Breast Cancer

APHINITY

The safety of PERJETA was evaluated in a multicenter, randomized, double-blind, placebo-controlled study (APHINITY) conducted in patients with HER2-positive early breast cancer who had their primary tumor excised prior to randomization [see Clinical Studies (14.3)].

Patients were randomized to receive either PERJETA in combination with trastuzumab and chemotherapy or placebo in combination with trastuzumab and chemotherapy. Investigators selected one of three anthracycline-based or non-anthracycline-based chemotherapy regimens for patients. PERJETA and trastuzumab were administered intravenously every 3 weeks starting on Day 1 of the first taxane-containing cycle, for a total of 52 weeks (up to 18 cycles) or until recurrence, withdrawal of consent, or unmanageable toxicity.

Serious adverse reactions (hospitalization) due to diarrhea in the PERJETA-treated group was 2.4%. The incidence of diarrhea was higher when chemotherapy was administered with PERJETA (61%) and was higher when administered with non-anthracycline based therapy (85%) than with anthracycline based therapy (67%). The median duration of diarrhea was 8 days. The median duration of Grade ≥3 diarrhea was 20 days. The incidence of diarrhea during the period PERJETA and trastuzumab were administered without chemotherapy was 18% in the PERJETA-treated group.

Adverse reactions resulting in permanent discontinuation of any study therapy were 13% for patients in the PERJETA-treated group. Adverse reactions resulting in permanent discontinuation of PERJETA was 7%. The most common adverse reactions (>0.5%) resulting in permanent discontinuation of any study treatment were ejection fraction decreased, neuropathy peripheral, diarrhea, and cardiac failure.

When PERJETA was administered in combination with trastuzumab and chemotherapy, the most common adverse reactions (> 30%) were diarrhea, nausea, alopecia, fatigue, peripheral neuropathy, and vomiting. The most common Grade 3 – 4 adverse reactions (> 2%) were neutropenia, febrile neutropenia, diarrhea, neutrophil count decreased, anemia, white blood cell count decreased, leukopenia, fatigue, nausea, and stomatitis.

Table 7 summarizes the adverse reactions that occurred in ≥ 10% of patients who received adjuvant PERJETA in combination with trastuzumab and chemotherapy followed by PERJETA and trastuzumab for a total of 52 weeks (up to 18 cycles) or until recurrence, withdrawal of consent, or unmanageable toxicity.

Table 7: Adverse Reactions (≥ 10%) of Patients Receiving Adjuvant PERJETA in Combination with Trastuzumab and Chemotherapy Followed by PERJETA and Trastuzumab in APHINITY
Adverse Reactions | PERJETA + trastuzumab + chemotherapy n=2364 % |  | Placebo + trastuzumab + chemotherapy n=2405 %
 | All Grades % | Grades 3 – 4 % | All Grades % | Grades 3 – 4 %
Gastrointestinal disorders
Diarrhea | 71 | 10 | 45 | 4
Nausea | 69 | 2 | 65 | 2
Vomiting | 32 | 2 | 30 | 2
Constipation | 29 | 0.5 | 32 | 0.3
Stomatitis | 28 | 2 | 24 | 1
Dyspepsia | 14 | 0 | 14 | 0
Abdominal pain | 12 | 0.5 | 11 | 0.6
Abdominal pain upper | 10 | 0.3 | 9 | 0.2
Skin and subcutaneous tissue disorders
Alopecia | 67 | <0.1 | 67 | <0.1
Rash | 26 | 0.4 | 20 | 0.2
Pruritus | 14 | 0.1 | 9 | <0.1
Dry skin | 13 | 0.1 | 11 | <0.1
Nail disorder | 12 | 0.2 | 12 | 0.1
General disorders and administration site conditions
Fatigue | 49 | 4 | 44 | 3
Mucosal inflammation | 23 | 2 | 19 | 0.7
Asthenia | 21 | 1 | 21 | 2
Pyrexia | 20 | 0.6 | 20 | 0.7
Edema peripheral | 17 | 0 | 20 | 0.2
Musculoskeletal and connective tissue disorders
Arthralgia | 29 | 0.9 | 33 | 1
Myalgia | 26 | 0.9 | 30 | 1
Pain in extremity | 10 | 0.2 | 10 | 0.2
Blood and lymphatic system disorders
Anemia | 28 | 7 | 23 | 5
Neutropenia | 25 | 16 | 23 | 16
Febrile neutropenia [In this table this denotes an adverse reaction that has been reported in association with a fatal outcome] | 12 | 12 | 11 | 11
Nervous system disorders
Dysgeusia | 26 | 0.1 | 22 | <0.1
Neuropathy peripheral | 33 | 1 | 32 | 1
Headache | 22 | 0.3 | 23 | 0.4
Paresthesia | 12 | 0.5 | 10 | 0.2
Dizziness | 11 | 0 | 11 | 0.2
Metabolism and nutrition disorders
Decreased appetite | 24 | 0.8 | 20 | 0.4
Vascular disorders
Hot flush | 20 | 0.2 | 21 | 0.4
Respiratory, thoracic, and mediastinal disorders
Epistaxis | 18 | <0.1 | 14 | 0
Cough | 16 | <0.1 | 15 | <0.1
Dyspnea | 12 | 0.4 | 12 | 0.5
Psychiatric disorders
Insomnia | 17 | 0.3 | 17 | <0.1
Investigations
Neutrophil count decreased | 14 | 10 | 14 | 10
Eye disorders
Lacrimation increased | 13 | 0 | 13 | <0.1
Infections and infestations
Nasopharyngitis | 13 | <0.1 | 12 | 0.1
Injury, poisoning and procedural complications
Radiation skin injury | 13 | 0.3 | 11 | 0.3

Clinically relevant adverse reactions in < 10% of patients who received PERJETA in combination with trastuzumab and anthracycline-based or non-anthracycline-based chemotherapy regimens included leukopenia, upper respiratory tract infection, and paronychia

Adverse Reactions in Patients Receiving PERJETA and Trastuzumab After Discontinuation of Chemotherapy

In APHINITY, adverse reactions that occurred after discontinuation of chemotherapy in >10% included diarrhea (18%), arthralgia (15%), radiation skin injury (12%), and hot flush (12%).

8 USE IN SPECIFIC POPULATIONS

8.1 Pregnancy

Pregnancy Pharmacovigilance Program

There is a pregnancy pharmacovigilance program for PERJETA. If PERJETA is administered during pregnancy, or if a patient becomes pregnant while receiving PERJETA or within 7 months following the last dose of PERJETA in combination with trastuzumab, health care providers and patients should immediately report PERJETA exposure to Genentech at 1-888-835-2555.

Risk Summary

Based on its mechanism of action and findings in animal studies, PERJETA can cause fetal harm when administered to a pregnant woman. There are no available data on the use of PERJETA in pregnant women. However, in post-marketing reports, use of another HER2/neu receptor antagonist (trastuzumab) during pregnancy resulted in cases of oligohydramnios and oligohydramnios sequence manifesting as pulmonary hypoplasia, skeletal abnormalities, and neonatal death. In an animal reproduction study, administration of pertuzumab to pregnant cynomolgus monkeys during the period of organogenesis resulted in oligohydramnios, delayed fetal kidney development, and embryo-fetal deaths at clinically relevant exposures that were 2.5 to 20-fold greater than exposures in humans receiving the recommended dose, based on Cmax [see Data]. Apprise the patient of the potential risks to a fetus. There are clinical considerations if PERJETA in combination with trastuzumab is used during pregnancy or within 7 months prior to conception [see Clinical Considerations].

The estimated background risk of major birth defects and miscarriage for the indicated population is unknown. In the U.S. general population, the estimated background risk of major birth defects and miscarriage in clinically recognized pregnancies is 2-4% and 15-20%, respectively.

Clinical Considerations

Fetal/Neonatal Adverse Reactions

Monitor women who received PERJETA in combination with trastuzumab during pregnancy or within 7 months prior to conception for oligohydramnios. If oligohydramnios occurs, perform fetal testing that is appropriate for gestational age and consistent with community standards of care.

Data

Animal Data

Pregnant cynomolgus monkeys were treated on Gestational Day (GD)19 with loading doses of 30 to 150 mg/kg pertuzumab, followed by bi-weekly doses of 10 to 100 mg/kg. These dose levels resulted in clinically relevant exposures of 2.5 to 20-fold greater than exposures in humans receiving the recommended dose, based on Cmax. Intravenous administration of pertuzumab from GD19 through GD50 (period of organogenesis) was embryotoxic, with dose-dependent increases in embryo-fetal death between GD25 to GD70. The incidences of embryo-fetal loss were 33, 50, and 85% for dams treated with bi-weekly pertuzumab doses of 10, 30, and 100 mg/kg, respectively (2.5 to 20-fold greater than the recommended human dose, based on Cmax). At Caesarean section on GD100, oligohydramnios, decreased relative lung and kidney weights, and microscopic evidence of renal hypoplasia consistent with delayed renal development were identified in all pertuzumab dose groups. Pertuzumab exposure was reported in offspring from all treated groups, at levels of 29% to 40% of maternal serum levels at GD100.

8.2 Lactation

Risk Summary

There is no information regarding the presence of pertuzumab in human milk, the effects on the breastfed infant or the effects on milk production. Published data suggest that human IgG is present in human milk but does not enter the neonatal and infant circulation in substantial amounts. Consider the developmental and health benefits of breast feeding along with the mother's clinical need for PERJETA treatment and any potential adverse effects on the breastfed child from PERJETA or from the underlying maternal condition. This consideration should also take into account the elimination half-life of pertuzumab and the trastuzumab wash out period of 7 months.

8.3 Females and Males of Reproductive Potential

Pregnancy Testing

Verify the pregnancy status of females of reproductive potential prior to the initiation of PERJETA.

Contraception

Females

Based on the mechanism of action and animal data, PERJETA can cause embryo-fetal harm when administered during pregnancy. Advise females of reproductive potential to use effective contraception during treatment and for 7 months following the last dose of PERJETA in combination with trastuzumab [see Use in Specific Populations (8.1)].

8.4 Pediatric Use

The safety and effectiveness of PERJETA have not been established in pediatric patients.

8.5 Geriatric Use

In CLEOPATRA, NeoSphere, TRYPHAENA, BERENICE, and APHINITY, 464 patients who received PERJETA were ≥ 65 years of age and 47 were ≥ 75 years of age.

The incidence of adverse reactions was increased in patients aged ≥ 65 years of age compared to patients aged < 65 years of age for decreased appetite, anemia, decreased weight, asthenia, dysgeusia, peripheral neuropathy, and hypomagnesemia.

No overall differences in efficacy of PERJETA were observed in patients aged ≥ 65 and <65 years of age. Clinical studies did not include sufficient numbers of patients aged ≥ 75 years to determine if these patients respond differently than younger patients.

Based on a population pharmacokinetic analysis, no significant difference was observed in the pharmacokinetics of pertuzumab between patients < 65 years (n=306) and patients ≥ 65 years (n=175).

8.6 Renal Impairment

Dose adjustments of PERJETA are not needed in patients with mild (creatinine clearance [CLcr] 60 to 90 mL/min) or moderate (CLcr 30 to 60 mL/min) renal impairment. No dose adjustment can be recommended for patients with severe renal impairment (CLcr less than 30 mL/min) because of the limited pharmacokinetic data available [see Clinical Pharmacology (12.3)].

11 DESCRIPTION

Pertuzumab is a recombinant humanized monoclonal antibody and HER2/neu receptor antagonist that targets the extracellular dimerization domain (Subdomain II) of the human epidermal growth factor receptor 2 protein (HER2). Pertuzumab is produced by recombinant DNA technology in a mammalian cell (Chinese Hamster Ovary) culture. Pertuzumab has an approximate molecular weight of 148 kDa.

PERJETA (pertuzumab) injection is a sterile, preservative-free, clear to slightly opalescent, colorless to pale brown solution for intravenous infusion. Each single-dose vial contains 420 mg of pertuzumab,glacial acetic acid (9.2 mg), histidine (43.5 mg), polysorbate 20 (2.8 mg), and sucrose (575.1 mg) with a pH of 6.

12 CLINICAL PHARMACOLOGY

12.1 Mechanism of Action

Pertuzumab targets the extracellular dimerization domain (Subdomain II) of the human epidermal growth factor receptor 2 protein (HER2) and, thereby, blocks ligand-dependent heterodimerization of HER2 with other HER family members, including EGFR, HER3, and HER4. As a result, pertuzumab inhibits ligand-initiated intracellular signaling through two major signal pathways, mitogen-activated protein (MAP) kinase, and phosphoinositide 3-kinase (PI3K). Inhibition of these signaling pathways can result in cell growth arrest and apoptosis, respectively. In addition, pertuzumab mediates antibody-dependent cell-mediated cytotoxicity (ADCC).

While pertuzumab alone inhibited the proliferation of human tumor cells, the combination of pertuzumab and trastuzumab augmented anti-tumor activity in HER2-overexpressing xenograft models.

12.2 Pharmacodynamics

The exposure-response relationship and time course of pharmacodynamic response for the safety and effectiveness of PERJETA have not been fully characterized.

Cardiac Electrophysiology

The effect of pertuzumab with an initial dose of 840 mg followed by a maintenance dose of 420 mg every three weeks on QTc interval was evaluated in a subgroup of 20 patients with HER2-positive breast cancer in CLEOPATRA. At the recommended dose of PERJETA, a mean increase in the QTc interval >20 ms was not observed. A small increase in the mean QTc interval (i.e., less than 10 ms) cannot be excluded because of the limitations of the trial design.

12.3 Pharmacokinetics

Based on a population PK analysis that included 481 patients, pertuzumab demonstrated linear pharmacokinetics at a dose range of 2 – 25 mg/kg.

With an initial dose of 840 mg followed by a maintenance dose of 420 mg every three weeks thereafter, the steady-state concentration of pertuzumab was reached after the first maintenance dose.

Elimination

The median clearance (CL) of pertuzumab was 0.24 L/day and the median half-life was 18 days.

Specific Populations

No clinically significant differences in the pharmacokinetics of pertuzumab were observed based on age, sex, ethnicity (Japanese vs. non-Japanese), or disease status (neoadjuvant or adjuvant vs. metastatic setting). No dose adjustments based on body weight or baseline albumin level are needed, as the exposure changes are not considered clinically relevant.

Pertuzumab exposure in patients with mild (CLcr 60 to 90 mL/min, n=200) and moderate renal impairment (CLcr 30 to 60 mL/min, n=71) were similar to those in patients with normal renal function (CLcr greater than 90 mL/min, n=200). The pharmacokinetics of pertuzumab in patients with moderate to severe hepatic impairment or severe renal impairment is unknown.

12.6 Immunogenicity

The observed incidence of anti-drug antibodies (ADA) is highly dependent on the sensitivity and specificity of the assay. Differences in assay methods preclude meaningful comparisons of the incidence of ADA in the studies described below with the incidence of ADA in other studies, including those of PERJETA or of other pertuzumab products.

Patients in CLEOPATRA were tested at multiple time-points for anti-pertuzumab antibodies. 3% (13/389) of patients in the PERJETA-treated group and 7% (25/372) of patients in the placebo-treated group tested positive for anti-pertuzumab antibodies. Of these 38 patients, none experienced anaphylactic/hypersensitivity reactions that were clearly related to anti-pertuzumab antibodies. The presence of pertuzumab in patient serum at the levels expected at the time of ADA sampling can interfere with the ability of this assay to detect anti-pertuzumab antibodies. In addition, the assay may be detecting antibodies to trastuzumab. As a result, data may not accurately reflect the true incidence of anti-pertuzumab antibody development.

In the neoadjuvant period of BERENICE, 0.3% (1/383) of patients treated with PERJETA tested positive for anti-pertuzumab antibodies. This patient did not experience any anaphylactic/hypersensitivity reactions.

Because of limited immunogenicity data, the clinical impact of anti-pertuzumab antibodies is unknown. There was no identified clinically significant effect of anti-pertuzumab antibodies on the safety of PERJETA.

13 NONCLINICAL TOXICOLOGY

13.1 Carcinogenesis, Mutagenesis, Impairment of Fertility

Long-term studies in animals have not been performed to evaluate the carcinogenic potential of pertuzumab.

Studies have not been performed to evaluate the mutagenic potential of pertuzumab.

No specific fertility studies in animals have been performed to evaluate the effect of pertuzumab. No adverse effects on male and female reproductive organs were observed in repeat-dose toxicity studies of up to six months duration in cynomolgus monkeys.

14 CLINICAL STUDIES

14.1 Metastatic Breast Cancer

CLEOPATRA (NCT00567190) was a multicenter, double-blind, placebo-controlled trial of 808 patients with HER2-positive metastatic breast cancer. HER2 overexpression was defined as a score of 3+ IHC or FISH amplification ratio of 2.0 or greater as determined by a central laboratory. Patients were randomly allocated 1:1 to receive placebo plus trastuzumab and docetaxel or PERJETA plus trastuzumab and docetaxel. Randomization was stratified by prior treatment (prior or no prior adjuvant/neoadjuvant anti-HER2 therapy or chemotherapy) and geographic region (Europe, North America, South America, and Asia). Patients with prior adjuvant or neoadjuvant therapy were required to have a disease-free interval of greater than 12 months before trial enrollment.

PERJETA was given intravenously at an initial dose of 840 mg, followed by 420 mg every 3 weeks thereafter. Trastuzumab was given intravenously at an initial dose of 8 mg/kg, followed by 6 mg/kg every 3 weeks thereafter. Patients were treated with PERJETA and trastuzumab until progression of disease, withdrawal of consent, or unacceptable toxicity. Docetaxel was given as an initial dose of 75 mg/m^2 by intravenous infusion every 3 weeks for at least 6 cycles. The docetaxel dose could be escalated to 100 mg/m^2 at the investigator's discretion if the initial dose was well tolerated. At the time of the primary analysis, the mean number of cycles of study treatment administered was 16.2 in the placebo-treated group and 19.9 in the PERJETA-treated group.

The major efficacy outcome measure of CLEOPATRA was progression-free survival (PFS) as assessed by an independent review facility (IRF). PFS was defined as the time from the date of randomization to the date of disease progression or death (from any cause) if the death occurred within 18 weeks of the last tumor assessment. Additional endpoints included overall survival (OS), PFS (investigator-assessed), objective response rate (ORR), and duration of response.

Patient demographic and baseline characteristics were balanced between the treatment arms. The median age was 54 (range 22 to 89 years), 59% were White, 32% were Asian, and 4% were Black. All were female with the exception of 2 patients (0.2%). Seventeen percent (17%) of patients were enrolled in North America, 14% in South America, 38% in Europe, and 31% in Asia. Tumor prognostic characteristics, including hormone receptor status (positive 48%, negative 50%), presence of visceral disease (78%) and non-visceral disease only (22%) were similar in the study arms. Approximately half of the patients received prior adjuvant or neoadjuvant anti-HER2 therapy or chemotherapy (PERJETA 46%, placebo 47%). Among patients with hormone receptor positive tumors, 45% received prior adjuvant hormonal therapy and 11% received hormonal therapy for metastatic disease. Eleven percent of patients received prior adjuvant or neoadjuvant trastuzumab.

CLEOPATRA demonstrated a statistically significant improvement in IRF-assessed PFS in the PERJETA-treated group compared with the placebo-treated group. The results for investigator-assessed PFS were comparable to those observed for IRF-assessed PFS. A statistically significant OS improvement was demonstrated for the PERJETA-treated group compared with the placebo-treated group) with the final OS analysis. OS results in patient subgroups were consistent with those observed for IRF-assessed PFS with the exception of the subgroup of patients with disease limited to non-visceral metastasis [HR=1.11 (95% CI: 0.66, 1.85)].

Table 8: Efficacy Results from CLEOPATRA
Endpoint | PERJETA + trastuzumab + docetaxel n=402 | Placebo + trastuzumab + docetaxel n=406
Progression-Free Survival
(independent review)
Number of events (%) | 191 (47.5%) | 242 (59.6%)
Median (months) | 18.5 | 12.4
Hazard Ratio (95% CI) | 0.62 (0.51, 0.75)
p-value | < 0.0001
Overall Survival [Final analysis of overall survival performed when 389 patients had died.] (final)
Deaths (%) | 168 (41.8%) | 221 (54.4%)
Median (months) | 56.5 | 40.8
Hazard Ratio (95% CI) | 0.68 (0.56, 0.84)
p-value | 0.0002
Objective Response Rate (independent review) | n = 343 | n = 336
Objective response (CR + PR) | 275 (80.2%) | 233 (69.3%)
Complete response (CR) (%) | 19 (5.5%) | 14 (4.2%)
Partial Response (PR) (%) | 256 (74.6%) | 219 (65.2%)
Difference in ORR (95% CI) | 10.8% (4.2%, 17.5%)
p-value | 0.0011
Duration of Response Median (months) | 20.2 | 12.5
CI=Confidence Interval

Consistent results were observed across several patient subgroups including age (< 65 or ≥ 65 years), race, geographic region, prior adjuvant/neoadjuvant anti-HER2 therapy or chemotherapy (yes or no), and prior adjuvant/neoadjuvant trastuzumab (yes or no). In the subgroup of patients with hormone receptor-negative disease (n=408), the hazard ratio was 0.55 (95% CI: 0.42, 0.72). In the subgroup of patients with hormone receptor-positive disease (n=388), the hazard ratio was 0.72 (95% CI: 0.55, 0.95). In the subgroup of patients with disease limited to non-visceral metastasis (n=178), the hazard ratio was 0.96 (95% CI: 0.61, 1.52).

Figure 1 Kaplan-Meier Curve of Progression-Free Survival for CLEOPATRA (IRF-Assessed)

Figure 2 Kaplan-Meier Curve of Overall Survival for CLEOPATRA (Final Analysis)

14.2 Neoadjuvant Treatment of Breast Cancer

NeoSphere

NeoSphere (NCT00545688) was a multicenter, randomized trial conducted in 417 patients with operable, locally advanced, or inflammatory HER2-positive breast cancer (T2-4d) who were scheduled for neoadjuvant therapy. HER2 overexpression was defined as a score of 3+ IHC or FISH amplification ratio of 2.0 or greater as determined by a central laboratory. Patients were randomly allocated to receive 1 of 4 neoadjuvant regimens prior to surgery as follows: trastuzumab plus docetaxel, PERJETA plus trastuzumab and docetaxel, PERJETA plus trastuzumab, or PERJETA plus docetaxel. Randomization was stratified by breast cancer type (operable, locally advanced, or inflammatory) and estrogen receptor (ER) or progesterone receptor (PgR) positivity.

PERJETA was given intravenously at an initial dose of 840 mg, followed by 420 mg every 3 weeks for 4 cycles. Trastuzumab was given intravenously at an initial dose of 8 mg/kg, followed by 6 mg/kg every 3 weeks for 4 cycles. Docetaxel was given as an initial dose of 75 mg/m^2 by intravenous infusion every 3 weeks for 4 cycles. The docetaxel dose could be escalated to 100 mg/m^2 at the investigator's discretion if the initial dose was well tolerated. Following surgery all patients received 3 cycles of 5-fluorouracil (600 mg/m^2), epirubicin (90 mg/m^2), and cyclophosphamide (600 mg/m^2) (FEC) given intravenously every 3 weeks and trastuzumab administered intravenously every 3 weeks to complete 1 year of therapy. After surgery, patients in the PERJETA plus trastuzumab arm received docetaxel every 3 weeks for 4 cycles prior to FEC.

The major efficacy outcome measure was pathological complete response (pCR) rate in the breast (ypT0/is) defined as the absence of invasive cancer in the breast and lymph nodes (ypT0/is ypN0) for the efficacy analysis.

Demographics were balanced (median age was 49 – 50 years old, the majority were White (71%) and all were female. Overall, 7% of patients had inflammatory cancer, 32% had locally advanced cancer, and 61% had operable cancer. Approximately half the patients in each treatment group had hormone receptor-positive disease (defined as ER-positive and/or PgR-positive).

Statistically significant improvements in pCR rates were observed in patients receiving PERJETA plus trastuzumab and docetaxel compared to patients receiving trastuzumab plus docetaxel. The pCR rates and magnitude of improvement with PERJETA were lower in the subgroup of patients with hormone receptor-positive tumors compared to patients with hormone receptor-negative tumors. The efficacy results are summarized in Table 9.

Table 9: Efficacy Results from NeoSphere
Endpoint | H+T N=107 | Ptz+H+T N=107 | Ptz+H N=107 | Ptz+T N=96
pCR [ypT0/is ypN0 (absence of invasive cancer in the breast and lymph nodes) based on intention-to-treat population] , n (%) [95% CI] [95% CI for one sample binomial using Pearson-Clopper method.] | 23 (21.5%) [14.1, 30.5] | 42 (39.3%) [30.0, 49.2] | 12 (11.2%) [5.9, 18.8] | 17 (17.7%) [10.7, 26.8]
p-value (with Simes correction for CMH test) [p-value from Cochran-Mantel-Haenszel (CMH) test, with Simes multiplicity adjustment] |  | 0.0063 (vs. H+T) | 0.0223 (vs. H+T) | 0.0018 (vs. Ptz+H+T)
Hormone receptor-positive subgroup | N=50 | N=50 | N=51 [One patient had unknown hormone receptor status. The patient did not achieve a pCR.] | N=46
pCR, n (%) [95% CI] | 6 (12.0%) [4.5, 24.3] | 11 (22.0%) [11.5, 36.0] | 1 (2.0%) [0.1, 10.5] | 4 (8.7%) [2.4, 20.8]
Hormone receptor-negative subgroup | N=57 | N=57 | N=55 | N=50
pCR, n (%) [95% CI] | 17 (29.8%) [18.4, 43.4] | 31 (54.4%) [40.7, 67.6] | 11 (20.0%) [10.4, 33.0] | 13 (26.0%) [14.6, 40.3]
T=docetaxel, Ptz=PERJETA, H=trastuzumab
CI=Confidence Interval

TRYPHAENA

TRYPHAENA(NCT00976989) was a three-arm, randomized (1:1:1) study in the neoadjuvant setting conducted in 225 patients with HER2-positive locally advanced, operable, or inflammatory (T2-4d) breast cancer designed primarily to assess cardiac safety. HER2 overexpression was defined as a score of 3+ IHC or FISH amplification ratio of 2.0 or greater as determined by a central laboratory.

Patients were randomly allocated to receive 1 of 3 neoadjuvant regimens prior to surgery as follows: 3 cycles of FEC followed by 3 cycles of docetaxel all in combination with PERJETA and trastuzumab, 3 cycles of FEC alone followed by 3 cycles of docetaxel and trastuzumab in combination with PERJETA, or 6 cycles of docetaxel, carboplatin, and trastuzumab (TCH) in combination with PERJETA. Randomization was stratified by breast cancer type (operable, locally advanced, or inflammatory) and ER and/or PgR positivity.

PERJETA was given by intravenous infusion at an initial dose of 840 mg, followed by 420 mg every 3 weeks. Trastuzumab was given by intravenous infusion at an initial dose of 8 mg/kg, followed by 6 mg/kg every 3 weeks. 5-Fluorouracil (500 mg/m^2), epirubicin (100 mg/m^2), and cyclophosphamide (600 mg/m^2) [FEC] were given intravenously every 3 weeks for 3 cycles. In the PERJETA plus trastuzumab, docetaxel, and FEC arms, docetaxel was given as an initial dose of 75 mg/m^2 by intravenous infusion every 3 weeks for 3 cycles with the option to escalate to 100 mg/m^2 at the investigator's discretion if the initial dose was well tolerated. However, in the PERJETA plus TCH arm, docetaxel was given intravenously at 75 mg/m^2 (no escalation was permitted) and carboplatin (AUC 6) was given intravenously every 3 weeks for 6 cycles. Following surgery all patients received trastuzumab to complete 1 year of therapy, which was administered intravenously every 3 weeks.

Demographics were balanced (median age was 49-50 years old, the majority were White [76%]) and all were female. Overall 6% of patients had inflammatory cancer, 25% had locally advanced cancer and 69% had operable cancer, with approximately half the patients in each treatment group having ER-positive and/or PgR-positive disease.

The pCR (ypT0/is ypN0) rates were 56.2% (95% CI: 44.1%, 67.8%), 54.7% (95% CI: 42.7%, 66.2%), and 63.6% (95% CI: 51.9%, 74.3%) for patients treated with PERJETA plus trastuzumab and FEC followed by PERJETA plus trastuzumab and docetaxel, PERJETA plus trastuzumab and docetaxel following FEC, or PERJETA plus TCH, respectively. The pCR rates were lower in the subgroups of patients with hormone receptor-positive tumors: 41.0% (95% CI: 25.6%, 57.9%), 45.7% (95% CI: 28.8%, 63.4%), and 47.5% (95% CI: 31.5%, 63.9%) than with hormone receptor-negative tumors: 73.5% (95% CI: 55.6%, 87.1%), 62.5% (95% CI: 45.8%, 77.3%), and 81.1% (95% CI: 64.8%, 92.0%), respectively.

BERENICE

A two-arm non-randomized study (BERENICE, NCT02132949) was conducted in 401 patients with HER2-positive locally advanced, inflammatory, or early-stage HER2-positive breast cancer. HER2 overexpression was defined as a score of 3+ IHC or ISH amplification ratio of 2.0 or greater as determined by a central laboratory.

Patients received 1 of 2 neoadjuvant regimens prior to surgery as follows: 4 cycles of dose dense doxorubicin and cyclophosphamide (ddAC) followed by 4 cycles of PERJETA in combination with trastuzumab and weekly paclitaxel for 12 weeks or 4 cycles of 5-fluorouracil, epirubicin and cyclophosphamide (FEC) followed by 4 cycles of PERJETA in combination with trastuzumab and docetaxel. The choice of neoadjuvant treatment regimen was made by the Investigator on a site-specific basis. Dosing for the regimens was as follows:

- PERJETA was given by intravenous infusion at an initial dose of 840 mg, followed by 420 mg every 3 weeks. Trastuzumab was given by intravenous infusion at an initial dose of 8 mg/kg, followed by 6 mg/kg every 3 weeks.
- In the ddAC cohort, (doxorubicin 60 mg/m^2 and cyclophosphamide 600 mg/m^2) were given intravenously every 2 weeks (ddAC) for 4 cycles with G-CSF (granulocyte colony stimulating factor) support at investigator discretion, followed by paclitaxel 80 mg/m^2 given intravenously weekly for 12 weeks, with PERJETA and trastuzumab every 3 weeks from the start of paclitaxel for 4 cycles.
- In the FEC cohort, 5-Fluorouracil (5-FU) (500 mg/m^2), epirubicin (100 mg/m^2), and cyclophosphamide (600 mg/m^2) were given intravenously every 3 weeks for 4 cycles, followed by docetaxel given as an initial dose of 75 mg/m^2 by intravenous infusion every 3 weeks for 4 cycles with PERJETA and trastuzumab, and with the option to escalate to 100 mg/m^2 at the investigator's discretion if the initial dose was well tolerated.

Following surgery, all patients received PERJETA and trastuzumab administered intravenously every 3 weeks to complete 1 year of therapy.

The median age was 49 years old (range 21-78), 12% of patients were 65 or older, 83% were White, and all but one patient was female (99.8%). Overall 3% of patients had inflammatory cancer, 23% had locally advanced cancer (Stage 3A or greater), 5% were not classified per TNM staging, with approximately two thirds of the patients in each treatment group having ER-positive and/or PgR-positive disease. All patients had an ECOG performance status of 0 or 1.

The pCR (ypT0/is ypN0) rates were 61.8% (95% CI: 54.7, 68.6) and 60.7% (95% CI: 53.6, 67.5) for patients treated with ddAC followed by PERJETA plus trastuzumab and paclitaxel, or FEC followed by PERJETA plus trastuzumab and docetaxel, respectively. The pCR rates were lower in the subgroups of patients with hormone receptor-positive tumors: 51.6% (95% CI: 42.6, 60.5%) and 57.3% (95% CI: 48.1, 66.1%) than with hormone receptor-negative tumors: 81.5% (95% CI: 70.0, 90.1%) and 68.0% (95% CI: 56.2, 78.3%), respectively.

14.3 Adjuvant Treatment of Breast Cancer

APHINITY (NCT01358877) was a multicenter, randomized, double-blind, placebo-controlled study conducted in 4804 patients with HER2-positive early breast cancer who had their primary tumor excised prior to randomization. Patients were then randomized to receive PERJETA or placebo, in combination with adjuvant trastuzumab and chemotherapy. Randomization was stratified by the following factors: region, nodal status, protocol version, central hormone receptor status, and adjuvant chemotherapy regimen.

Investigators selected one of the following anthracycline-based or non-anthracycline-based chemotherapy regimens for individual patients:

- 3 or 4 cycles of FEC (5-FU 500-600 mg/m^2, epirubicin 90-120 mg/m^2, cyclophosphamide 500-600 mg/m^2) or FAC (5-FU 500-600 mg/m^2, doxorubicin 50 mg/m^2, cyclophosphamide 500-600 mg/m^2), followed by 3 or 4 cycles of docetaxel (75 mg/m^2 which could be escalated to 100 mg/m^2 every 3 weeks) or 12 cycles of weekly paclitaxel (80 mg/m^2).
- 4 cycles of AC (doxorubicin 60 mg/m^2 and cyclophosphamide 500-600 mg/m^2) or EC (epirubicin 90-120 mg/m^2 and cyclophosphamide 500-600 mg/m^2) either every 3 weeks or every 2 weeks with GCSF support, followed by docetaxel (100 mg/m^2 for 3 cycles or 75 mg/m^2 for first cycle and 100 mg/m^2 for subsequent three cycles, or 75 mg/m^2 for four cycles) or 12 cycles of weekly paclitaxel (80 mg/m^2).
- 6 cycles of docetaxel (75 mg/m^2) in combination with carboplatin (AUC 6)

PERJETA and trastuzumab were administered intravenously every 3 weeks starting on Day 1 of the first taxane-containing cycle, for a total of 52 weeks (up to 18 cycles) or until recurrence, withdrawal of consent, or unmanageable toxicity.

After completion of chemotherapy, patients received radiotherapy and/or hormone therapy as per investigator's discretion.

The major efficacy outcome of the study was invasive disease-free survival (IDFS), defined as the time from randomization to first occurrence of ipsilateral local or regional invasive breast cancer recurrence, distant recurrence, contralateral invasive breast cancer, or death from any cause. Additional efficacy endpoints were IDFS including second primary non-breast cancer, disease-free survival (DFS), and overall survival (OS).

Demographics were balanced between the two treatment arms. The median age was 51 years (range 18-86), 13% of patients were 65 or older, and over 99% of patients were female. Sixty-three percent of patients had node-positive disease, 64% had hormone receptor-positive disease, and 71% were White. All patients had an ECOG performance status of 0 or 1. Seventy-eight percent received an anthracycline containing regimen.

PERJETA-treated patients and placebo-treated patients both received a median number of 18 cycles of anti-HER2 therapy. After a median follow-up of 45.4 months, a statistically significant improvement in IDFS was demonstrated in patients randomized to receive PERJETA compared with patients randomized to receive placebo. The efficacy results from APHINITY are summarized in Tables 10 and 11 and in Figure 3.

Table 10: Efficacy Results from APHINITY
 | PERJETA + trastuzumab + chemotherapy N=2400 | Placebo + trastuzumab + chemotherapy N=2404
Invasive Disease Free Survival (IDFS)
Number (%) of patients with event | 171 (7.1%) | 210 (8.7%)
HR [95% CI] [All analyses stratified by nodal status, protocol version, central hormone receptor status, and adjuvant chemotherapy regimen. Stratification factors are defined according to the randomization data for IDFS.] | 0.82 [0.67, 1.00]
p-value (Log-Rank test, stratified) | 0.047
3 year event-free rate [3-year event-free rate derived from Kaplan-Meier estimates] , % [95% CI] | 94.1 [93.1, 95.0] | 93.2 [92.2, 94.3]
IDFS including second primary non-breast cancer
Number (%) of patients with event | 189 (7.9%) | 230 (9.6%)
HR [95% CI] | 0.83 [0.68, 1.00]
3 year event-free rate, % [95% CI] | 93.5 [92.5, 94.5] | 92.5 [91.4, 93.6]
Disease Free Survival (DFS)
Number (%) of patients with event | 192 (8.0%) | 236 (9.8%)
HR [95% CI] | 0.82 [0.68, 0.99]
3 year event-free rate, % [95% CI] | 93.4 [92.4, 94.4] | 92.3 [91.2, 93.4]
Overall Survival (OS) [Data from first interim analysis]
Number (%) of patients with event | 80 (3.3%) | 89 (3.7%)
HR [95% CI] | 0.89 [0.66, 1.21]
3 year event-free rate, % [95% CI] | 97.7 [97.0, 98.3] | 97.7 [97.1, 98.3]
HR=Hazard Ratio, CI=Confidence Interval

Figure 3 Kaplan-Meier Curve of Invasive Disease Free Survival from APHINITY (ITT Population)

Table 11 Efficacy Results by Baseline Disease Characteristics and Adjuvant Chemotherapy from APHINITY [Exploratory analyses without adjusting multiple comparisons, therefore, results are considered descriptive.]
Population | Number of events/Total N (%) |  | IDFS at 3 year (%, 95% CI) |  | Unstratified HR (95% CI)
Population | PERJETA + trastuzumab + chemotherapy | Placebo + trastuzumab + chemotherapy | PERJETA + trastuzumab + chemotherapy | Placebo + trastuzumab + chemotherapy | Unstratified HR (95% CI)
Hormone Receptor Status
Negative | 71/864 (8.2%) | 91/858 (10.6%) | 92.8 (90.8, 94.3) | 91.2 (89.0, 92.9) | 0.76 (0.56, 1.04)
Positive | 100/1536 (6.5%) | 119/1546 (7.7%) | 94.8 (93.5, 95.8) | 94.4 (93.1, 95.4) | 0.86 (0.66, 1.13)
Nodal Status
Negative | 32/897 (3.6%) | 29/902 (3.2%) | 97.5 (96.3, 98.4) | 98.4 (97.3, 99.0) | 1.13 (0.68, 1.86)
Positive | 139/1503 (9.2%) | 181/1502 (12.1%) | 92.0 (90.5, 93.3) | 90.2 (88.5, 91.6) | 0.77 (0.62, 0.96)
Adjuvant Chemotherapy Regimen
Anthracycline | 139/1865 (7.4%) | 171/1877 (9.1%) | 93.8 (92.6, 94.8) | 93.0 (91.8, 94.1) | 0.82 (0.66, 1.03)
Non-Anthracycline | 32/535 (6.0%) | 39/527 (7.4%) | 94.9 (92.6, 96.6) | 94.0 (91.5, 95.8) | 0.82 (0.51, 1.31)

16 HOW SUPPLIED/STORAGE AND HANDLING

How Supplied

PERJETA (pertuzumab) injection is supplied as a 420 mg/14 mL (30 mg/mL) single-dose vial containing sterile, preservative-free, clear to slightly opalescent, colorless to pale brown solution. NDC 50242-145-01.

Storage and Handling

Store vials refrigerated at 2°C to 8°C (36°F to 46°F) in the original carton until time of use to protect from light.

Do not freeze. Do not shake.

DO NOT FREEZE. DO NOT SHAKE.

17 PATIENT COUNSELING INFORMATION

Left Ventricular Dysfunction

- Advise patients to contact a health care professional immediately for any of the following: new onset or worsening shortness of breath, cough, swelling of the ankles/legs, swelling of the face, palpitations, weight gain of more than 5 pounds in 24 hours, dizziness or loss of consciousness [see Warnings and Precautions (5.1)].

Embryo-Fetal Toxicity

- Advise pregnant women and females of reproductive potential that exposure to PERJETA in combination with trastuzumab during pregnancy or within 7 months prior to conception can result in fetal harm [see Warnings and Precautions (5.2)]. Advise female patients to contact their healthcare provider with a known or suspected pregnancy [see Use in Specific Populations (8.1)].
- Advise women who are exposed to PERJETA in combination with trastuzumab during pregnancy or within 7 months prior to conception that there is a pregnancy pharmacovigilance program that monitors pregnancy outcomes. Encourage these patients to report their pregnancy to Genentech [see Use in Specific Populations (8.1)].
- Advise females of reproductive potential to use effective contraception during treatment and for 7 months following the last dose of PERJETA in combination with trastuzumab [see Use in Specific Populations (8.3)].

Hypersensitivity and Anaphylaxis

- Advise patients to contact their healthcare provider immediately and to report any symptoms of hypersensitivity or anaphylaxis including angioedema, breathing problems, or chest pain [see Warnings and Precautions (5.4)].

PERJETA® (pertuzumab)

Manufactured by:
Genentech, Inc.
A Member of the Roche Group
1 DNA Way
South San Francisco, CA 94080-4990
U.S. License No. 1048

PERJETA is a registered trademark of Genentech, Inc.
©2025 Genentech, Inc.

PRINCIPAL DISPLAY PANEL - 14 mL Vial Carton

NDC 50242-145-01

Perjeta®
(Pertuzumab)
Injection

420 mg/ 14 mL
(30 mg/mL)

Dilute Prior To Use
For Intravenous Infusion Only
Single-Dose Vial
Discard Unused Portion
No preservative.

Rx only

1 vial
Genentech

11029352